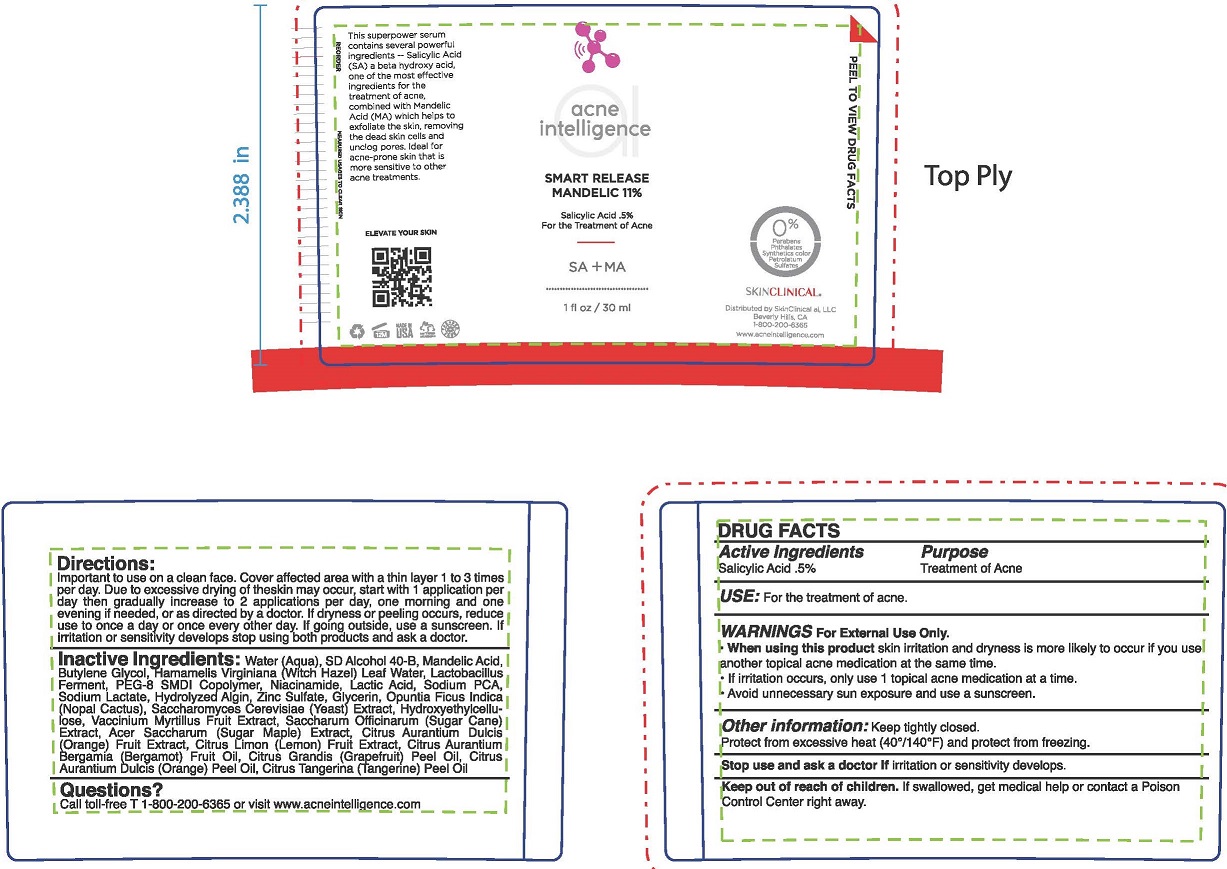 DRUG LABEL: Smart Release Mandelic
NDC: 73110-104 | Form: GEL
Manufacturer: SkinClinical AI, LLC
Category: otc | Type: HUMAN OTC DRUG LABEL
Date: 20190629

ACTIVE INGREDIENTS: SALICYLIC ACID 0.5 g/100 mL
INACTIVE INGREDIENTS: WATER; ALCOHOL; MANDELIC ACID; BUTYLENE GLYCOL; WITCH HAZEL; LACTOBACILLUS REUTERI; PEG-8/SMDI COPOLYMER; NIACINAMIDE; LACTIC ACID; SODIUM PYRROLIDONE CARBOXYLATE; SODIUM LACTATE; SODIUM ALGINATE; ZINC SULFATE; GLYCERIN; OPUNTIA FICUS-INDICA; YEAST, UNSPECIFIED; HYDROXYETHYL CELLULOSE (100 MPA.S AT 2%); BILBERRY; SACCHARUM OFFICINARUM WHOLE; ORANGE; LEMON; BERGAMOT OIL; CITRUS MAXIMA FRUIT RIND OIL; ORANGE OIL; MANDARIN OIL

Smart Release Mandelic 11%

ACTIVE INGREDIENT

SALICYLIC ACID .5%

PURPOSE

TREATMENT OF ACNE

WARNINGS

For External Use Only.

When using this product skin irritation and dryness is more likely to occur if you use another topical acne medication at the same time.

If irritation occurs, only use 1 topical acne medication at a time.

Avoid unnecessary sun exposure and use a sunscreen.

USE

HELPS PREVENT SUNBURN. IF USED WITH OTHER SUN PROTECTION MEASURES (SEE DIRECTIONS) DECREASES THE CHANCES OF SKIN CANCER AND EARLY SIGNES OF SKIN AGING CAUSED BY THE SUN.

OTHER INFORMATION

Keep tightly closed.
Protect from excessive heat (40°/ 140° F) and protect from freezing.

Stop use and ask a doctor if irritation or sensitivity develops.

Keep out of reach of children. If swallowed, get medical help or contact a Poisorl fontrol Center right away.

DIRECTIONS

Important to use on a clean face, Cover the affected area with a thin layer 1 to 3 times per day. Because of excessive drying of the skin may occur, start with 1 application per day then gradually increase to 2 applications per day, one morning and one evening ff needed, or as directed by a doctor. If dryness or peeling occurs, reduce use to once a day or once every other day. If going outside, use a sunscreen. if irritation or sensitivity develops stop using both products and ask a doctor.

INACTIVE INGREDIENTS

Water (Agua), SD Alcohol 40-B, Mandelic Acid, Butylene Glycol,Hamamelis Virginiana (Witch Hazel) Leaf Water, Lactobacillus Ferment, PEG-8 SMDI Copolymer, Niacinamide, Lactic Acid, Sodium PCA, Sodium Lactate, Hydrolyzed Algin, Zinc Sulfate, Glycerin, Opuntia Ficus lndica (Nopal Cactus), Saccharomyces Cerevisiae (Yeast) Extract, Hydroxyethylcellulose, Vaccinium Myrtillus Fruit Extract, Saccharum Officinarum (Sugar Cane) Extract, Acer Saccharum (Sugar Maple) Extract, Citrus Aurantium Dulcis (Orange) Fruit Extract, Citrus Limon (Lemon) Fruit Extract, Citrus Aurantium Bergamia (Bergamot) Fruit Oil, Citrus Grandis (Grapefruit) Peel Oi!, Citrus Aurantium Dulcis (Orange) Peel Oil, Citrus Tangerina (Tangerine) Peel Oil

Questions?

Call toll-free T 1-800-200-6365 or visit www.acneintellifillnce.com